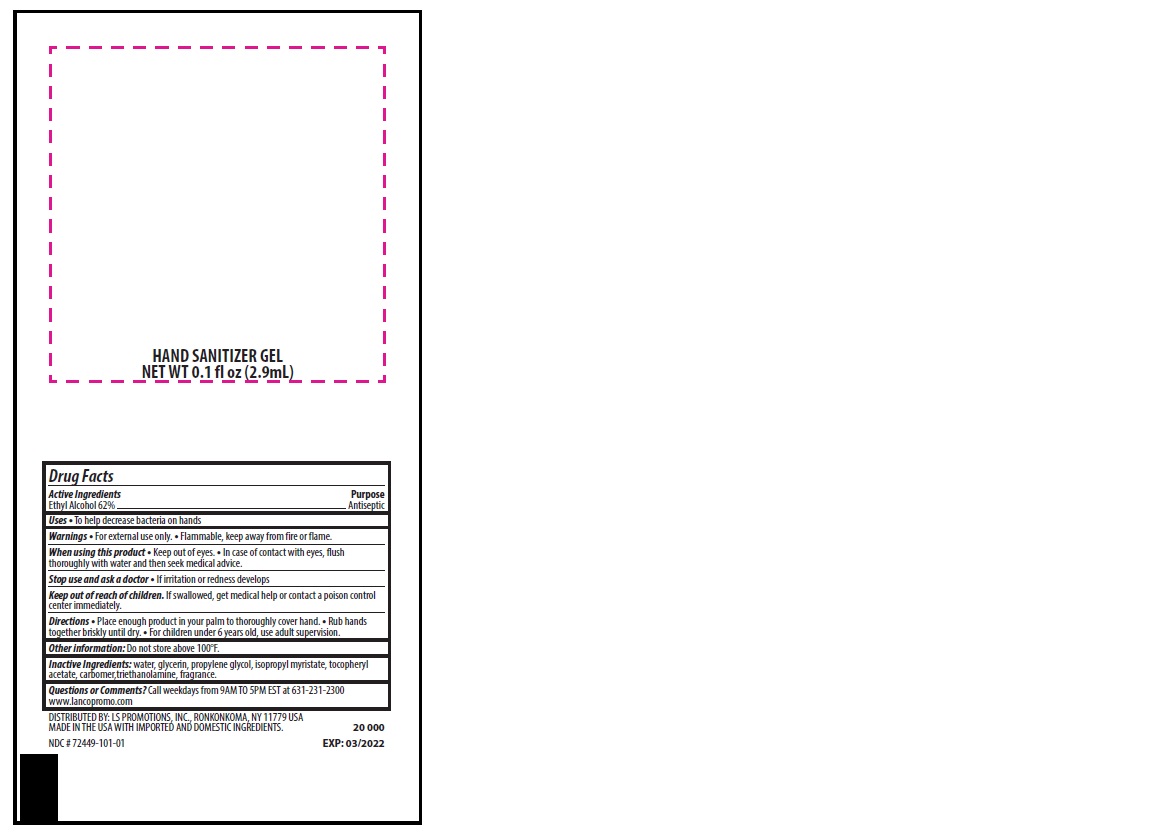 DRUG LABEL: Hand Sanitizer Gel
NDC: 72449-101 | Form: GEL
Manufacturer: LS Promotions Inc.
Category: otc | Type: HUMAN OTC DRUG LABEL
Date: 20200316

ACTIVE INGREDIENTS: ALCOHOL 0.62 mL/1 mL
INACTIVE INGREDIENTS: CARBOMER 1342; WATER; GLYCERIN; TROLAMINE; ISOPROPYL MYRISTATE; .ALPHA.-TOCOPHEROL ACETATE, D-; PROPYLENE GLYCOL

Hand Sanitizer Gel - Single Use Packet

Drug Facts

Active Ingredient

Ethanol 62%

PURPOSE

ANTISEPTIC

USES

TO HELP DECREASE BACTERIA ON HANDS

WARNINGS

FOR EXTERNAL USE ONLY. FLAMMABLE, KEEP AWAY FROM FIRE OR FLAME

WHEN USING THIS PRODUCT

KEEP OUT OF EYES. IN CASE OF CONTACT WITH EYES, FLUSH THOROUGHLY WITH WATER AND THEN SEEK MEDICAL ADVICE.

STOP USE AND ASK A DOCTOR

IF IRRITATION OR REDNESS DEVELOPS

KEEP OUT OF REACH OF CHILDREN

IF SWALLOWED, GET MEDICAL HELP OR CONTACT A POISON CONTROL CENTER IMMEDIATELY.

DIRECTIONS

PLACE ENOUGH PRODUCT IN YOUR PALM TO THOROUGHLY COVER HAND. RUB HANDS TOGETHER BRISKLY UNTIL DRY. FOR CHILDREN UNDER 6 YEARS OLD, USE ADULT SUPERVISION.

OTHER INFORMATION

DO NOT STORE ABOVE 100° F.

INACTIVE INGREDIENTS

Inactive Ingredients: water, glycerin, propylene glycol, isopropyl myristate, tocopheryl acetate, carbomer, triethanolamine, fragrance

QUESTIONS OR COMMENTS?

CALL WEEKDAYS FROM 9AM TO 5PM EST AT 631-231-2300
WWW.LANCOPROMO.COM